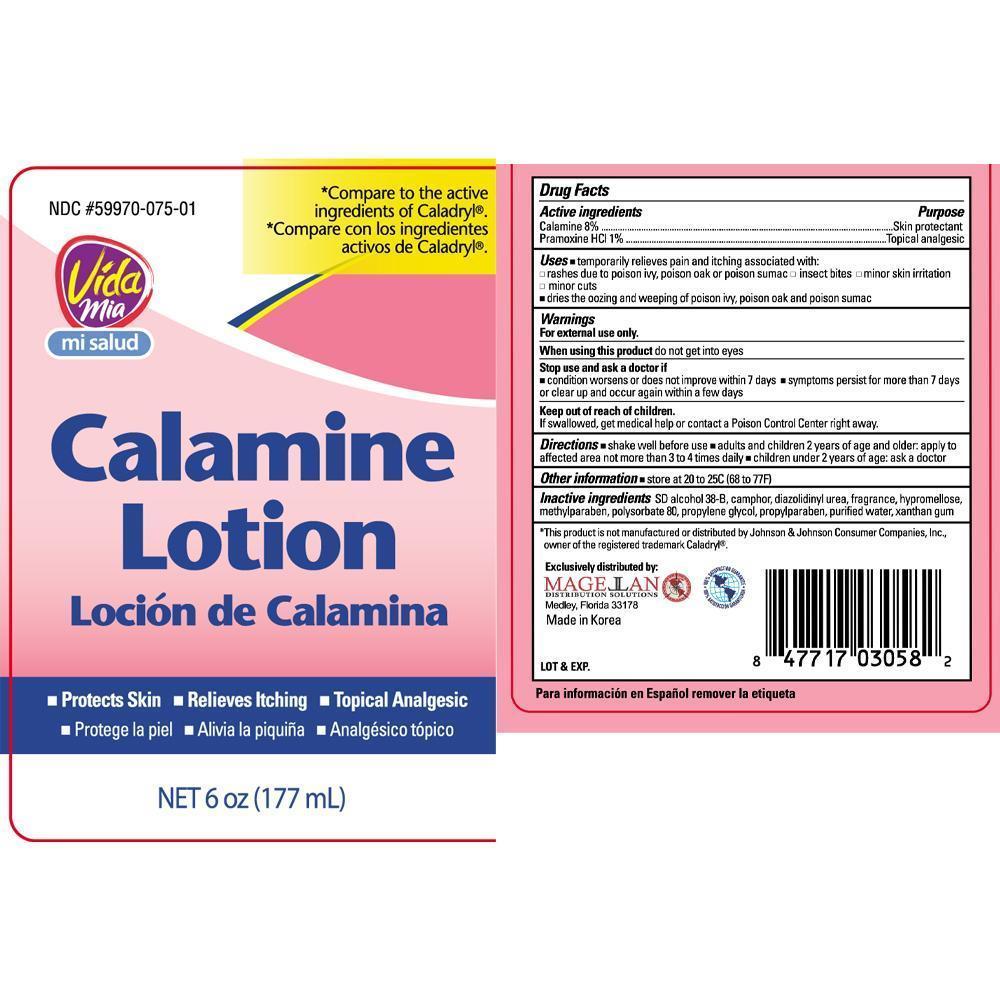 DRUG LABEL: Calamine
NDC: 59970-075 | Form: LOTION
Manufacturer: Navarro Discount Pharmacies, LLC
Category: otc | Type: HUMAN OTC DRUG LABEL
Date: 20130506

ACTIVE INGREDIENTS: ZINC OXIDE 80 mg/1 mL; FERRIC OXIDE RED 80 mg/1 mL; PRAMOXINE HYDROCHLORIDE 10 mg/1 mL
INACTIVE INGREDIENTS: ALCOHOL; CAMPHOR (NATURAL); HYPROMELLOSES; METHYLPARABEN; POLYSORBATE 80; PROPYLENE GLYCOL; PROPYLPARABEN; WATER; XANTHAN GUM

Drug Facts

Active ingredients

Calamine 8%

Pramoxine HCl 1%

Purpose

Skin protectant

Topical analgesic

Uses

temporarily relieves pain and itching associated with:

- rashes due to poison ivy, poison oac or poison sumac
- insect bites
- minor skin irritation
- minor cuts

dries the oozing and weeping of poison ivy, poison oak and poison sumac

Warnings

For external use only.

When using this product

do not get into eyes

Stop use and ask a doctor if

- condition worsens or does not improve within 7 days
- symptoms persist for more than 7 days or clear up and occur again within a few days

Keep out of reach of children.

If swallowed, get medical help or contact a Poison Control Center right away.

Directions

- shake well before use
- adults and children 2 years of age and older: apply to affected area not more than 3 to 4 times daily
- children under 2 years of age: ask a doctor

Other information

- store at 20° to 25°C (68° to 77°F)

Inactive ingredients

SD alcohol 38-B, camphor, diazolidinyl urea, fragrance, hypromellose, methylparaben, polysorbate 80, propylene glycol, propylparaben, purified water, zanthan gum